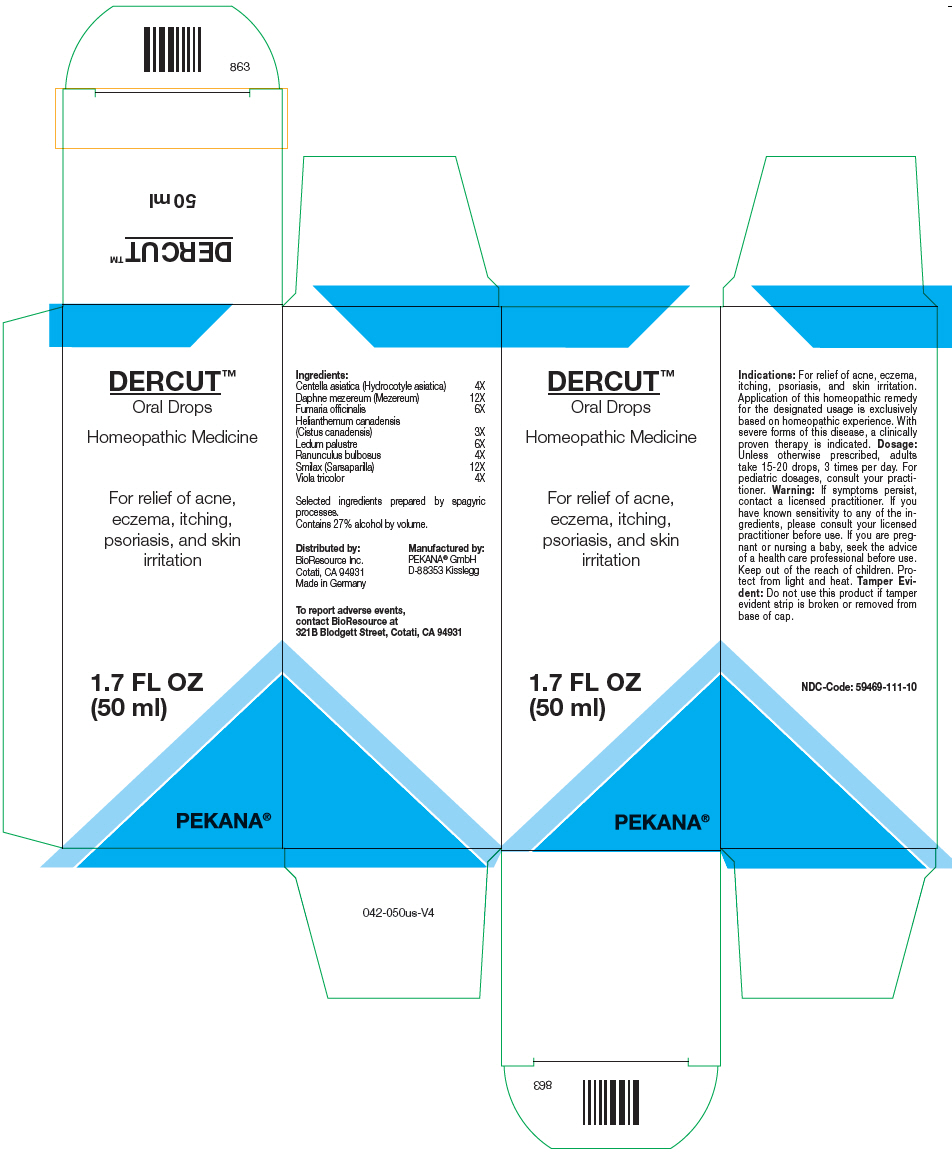 DRUG LABEL: DERCUT
NDC: 59469-111 | Form: SOLUTION/ DROPS
Manufacturer: PEKANA Naturheilmittel GmbH
Category: homeopathic | Type: HUMAN OTC DRUG LABEL
Date: 20221214

ACTIVE INGREDIENTS: Helianthemum canadense 3 [hp_X]/50 mL; Centella asiatica Flowering Top 4 [hp_X]/50 mL; Daphne mezereum Bark 12 [hp_X]/50 mL; RANUNCULUS BULBOSUS WHOLE 4 [hp_X]/50 mL; SMILAX ORNATA ROOT 12 [hp_X]/50 mL; Fumaria officinalis Flowering Top 6 [hp_X]/50 mL; RHODODENDRON TOMENTOSUM LEAFY TWIG 6 [hp_X]/50 mL; VIOLA TRICOLOR WHOLE 4 [hp_X]/50 mL
INACTIVE INGREDIENTS: Water; Alcohol

DERCUT™

ACTIVE INGREDIENT

Ingredients:
Centella asiatica (Hydrocotyle asiatica) | 4X
Daphne mezereum (Mezereum) | 12X
Fumaria officinalis | 6X
Helianthemum canadensis (Cistus canadensis) | 3X
Ledum palustre | 6X
Ranunculus bulbosus | 4X
Smilax (Sarsaparilla) | 12X
Viola tricolor | 4X

Selected ingredients prepared by spagyric processes.

INACTIVE INGREDIENT

Contains 27% alcohol by volume.

Indications

PURPOSE

For relief of acne, eczema, itching, psoriasis, and skin irritation. Application of this homeopathic remedy for the designated usage is exclusively based on homeopathic experience. With severe forms of this disease, a clinically proven therapy is indicated.

Dosage

Unless otherwise prescribed, adults take 15-20 drops, 3 times per day. For pediatric dosages, consult your practitioner.

Warning

ASK DOCTOR

If symptoms persist, contact a licensed practitioner. If you have known sensitivity to any of the ingredients, please consult your licensed practitioner before use. If you are pregnant or nursing a baby, seek the advice of a health care professional before use.

Keep out of the reach of children.

STORAGE AND HANDLING

Protect from light and heat.

Tamper Evident

Do not use this product if tamper evident strip is broken or removed from base of cap.

QUESTIONS

To report adverse events, contact BioResource at 321B Blodgett Street, Cotati, CA 94931

Distributed by:
BioResource Inc.
Cotati, CA 94931

Manufactured by:
PEKANA® GmbH
D-88353 Kisslegg

PRINCIPAL DISPLAY PANEL - 50 ml Bottle Box

DERCUT™
Oral Drops

Homeopathic Medicine

For relief of acne,
eczema, itching,
psoriasis, and skin
irritation

1.7 FL OZ
(50 ml)

PEKANA®